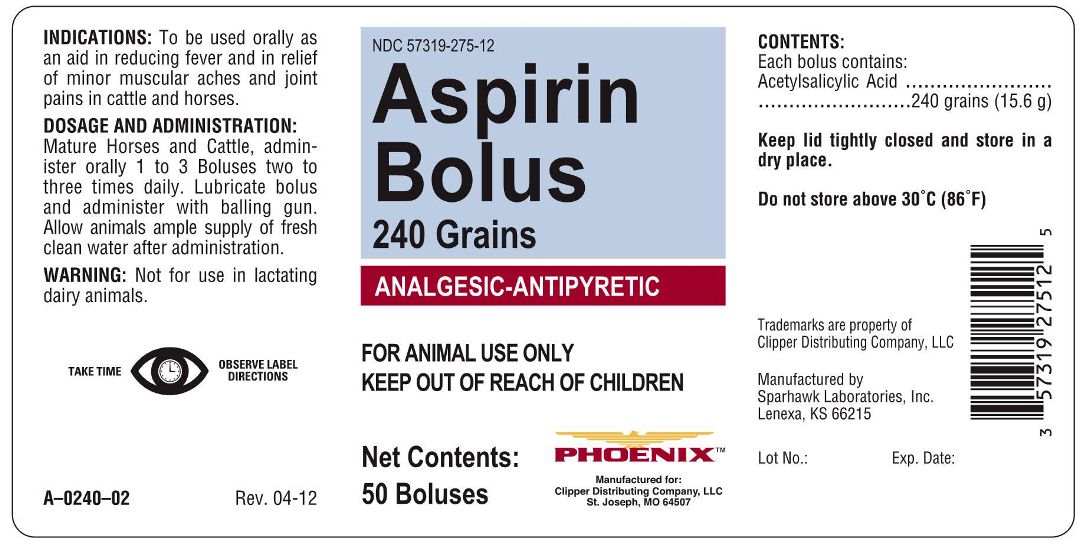 DRUG LABEL: ASPIRIN
NDC: 57319-275 | Form: PILL
Manufacturer: Clipper Distributing Company LLC
Category: animal | Type: OTC ANIMAL DRUG LABEL
Date: 20120605

ACTIVE INGREDIENTS: ASPIRIN 15.6 g/1 1

ASPIRIN BOLUSES 240 Grains ANALGESIC - ANTIPYRETIC

INDICATIONS

To be used orally as an aid in reducing fever and in relief of minor muscular aches and joint pains in cattle and horses.

DOSAGE AND ADMINISTRATION

Mature Horses and Cattle, administer orally 1 to 3 Boluses two to three times daily. Lubricate bolus and administer with balling gun. Allow animals ample supple of fresh clean water after administration.

WARNING

Not for use in lactating dairy animals.

CONTENTS

Each Bolus contains:

Acetylsalicylic Acid..........240 grains (15.6 g)

PACKAGE LABEL

FOR ANIMAL USE ONLY

KEEP OUT OF REACH OF CHILDREN